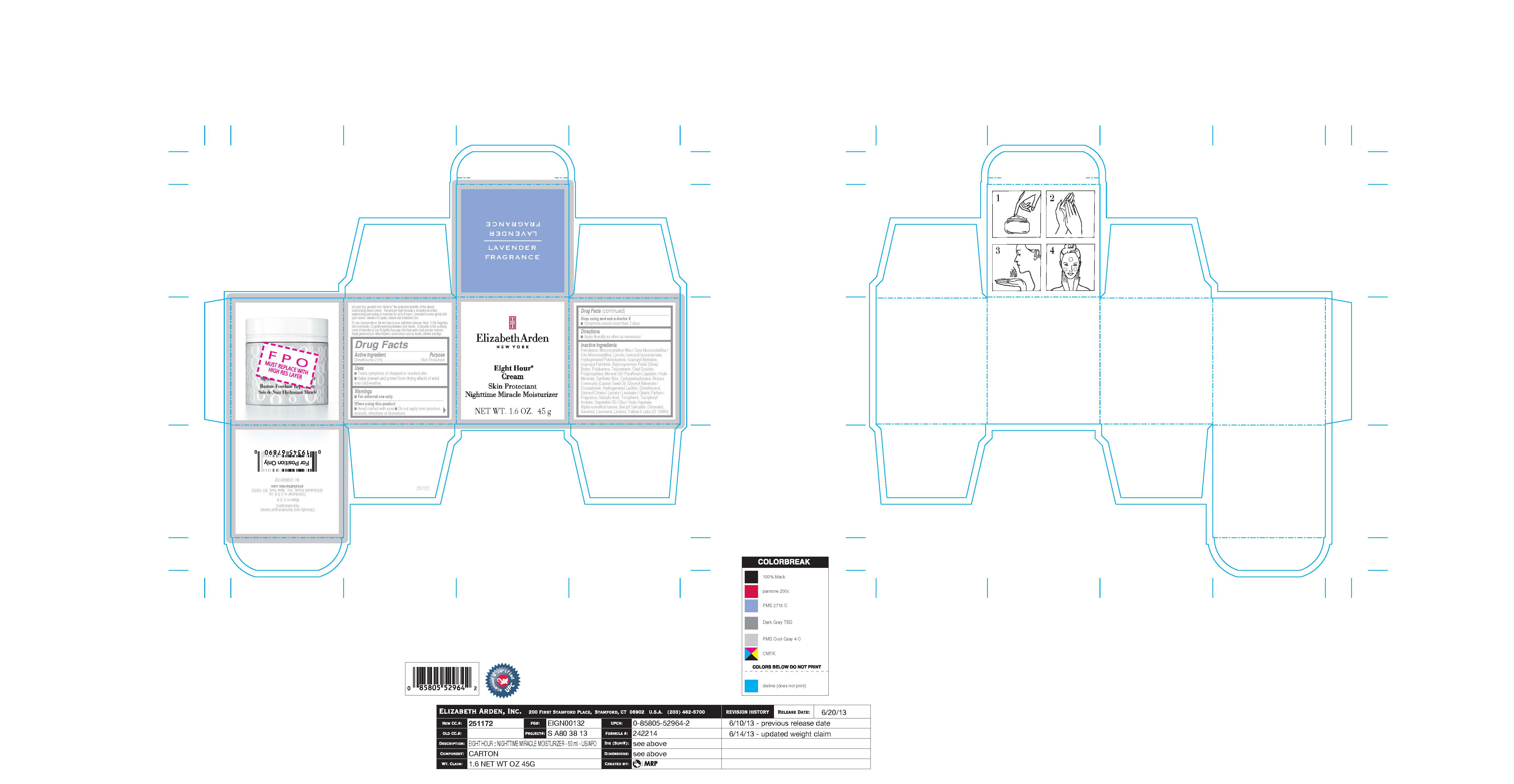 DRUG LABEL: EIGHT HOUR NIGHT
NDC: 10967-675 | Form: EMULSION
Manufacturer: REVLON
Category: otc | Type: HUMAN OTC DRUG LABEL
Date: 20240112

ACTIVE INGREDIENTS: DIMETHICONE 2 mg/1 g
INACTIVE INGREDIENTS: ISOPROPYL MYRISTATE; SALICYLIC ACID; .BETA.-CITRONELLOL, (R)-; LIMONENE, (+)-; GLYCERYL BEHENATE/EICOSADIOATE; ISOPROPYL PALMITATE; SYNTHETIC WAX (1200 MW); CYCLOMETHICONE 5; ISONONYL ISONONANOATE; HYDROGENATED POLYBUTENE (1300 MW); SHEA BUTTER; OLEYL ERUCATE; PETROLATUM; MINERAL OIL; TOCOPHEROL; CORN OIL; ISOMETHYL-.ALPHA.-IONONE; MICROCRYSTALLINE WAX; LANOLIN; DIMETHICONOL (100000 CST); GERANIOL; FD&C YELLOW NO. 6; ALPHA-TOCOPHEROL ACETATE; POLYPROPYLENE (30000 MW); HYDROGENATED SOYBEAN LECITHIN

ELIZABETH ARDEN EIGHT HOUR CREAM SKIN PROTECTANT NIGHTTIME MIRACLE MOISTURIZER

Active Ingredient

Active Ingredient Purpose
Dimethicone 2.0%...................................... Skin Protectant

Inactive Ingredients

PETROLATUM, MICROCRYSTALLINE WAX/CERA MICROCRISTALLINA/CIRE MICROCRISTALLINE, LANOLIN, ISONONYL ISONONANOATE, HYDROGENATED POLYISOBUTENE, ISOPROPYL MYRISTATE, ISOPROPYL PALMITATE, BUTYROSPERMUM PARKII (SHEA) BUTTER, POLYBUTENE, TRIISOSTEARIN, OLEYL ERUCATE, POLYPROPYLENE, MINERAL OIL/PARAFFINUM LIQUIDUM/HUILE MINERALE, SYNTHETIC WAX, CYCLOPENTASILOXANE, RICINUS COMMUNIS (CASTOR) SEED OIL, GLYCERYL BEHENATE/EICOSADIOATE, HYDROGENATED LECITHIN, DIMETHICONOL, GLYCERYL CITRATE/LACTATE/LINOLEATE/OLEATE, PARFUM/FRAGRANCE, SALICYLIC ACID, TOCOPHEROL, TOCOPHERYL ACETATE, VEGETABLE OIL/OLUS/HUILE VEGETALE, ALPHA-ISOMETHYL IONONE, BENZYL SALICYLATE, CITRONELLOL, GERANIOL, LIMONENE, LINALOOL, YELLOW 6 LAKE (CI 15985).

Uses and Directions

Uses
- Treats symptoms of chapped or cracked skin.
- Helps prevent and protect from drying effects of wind and cold weather.

Directions

- Apply liberally as often as necessary

Warnings

For external use only
When using this product
- Avoid contact with eyes

- Do not apply over puncture wounds, infections or lacerations

Stop using and ask a doctor if
- Symptoms persist more than 7 days

DOSAGE AND ADMINISTRATION

As Needed

INDICATIONS AND USAGE

- Treats symptoms of chapped or cracked skin
- Helps prevent and protect from drying effects of wind and cold weather

PURPOSE

Skin Protectant

Keep out of reach of children